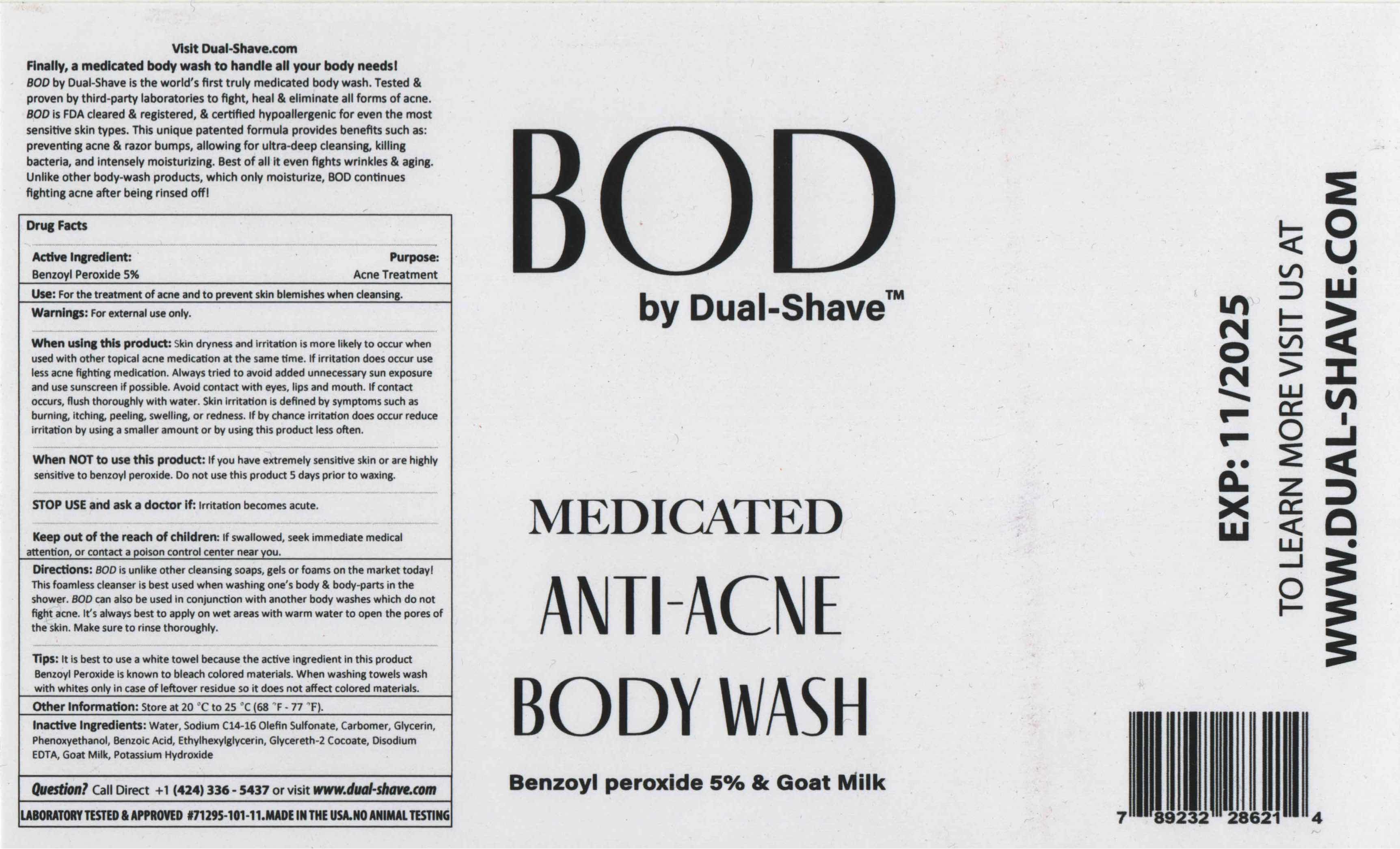 DRUG LABEL: BOD
NDC: 71295-104 | Form: LOTION
Manufacturer: Lamden, Nisan
Category: otc | Type: HUMAN OTC DRUG LABEL
Date: 20240109

ACTIVE INGREDIENTS: BENZOYL PEROXIDE 5 g/100 g
INACTIVE INGREDIENTS: WATER; MYRISTIC ACID; SODIUM C14-16 OLEFIN SULFONATE; COCAMIDOPROPYL BETAINE; STEARIC ACID; CARBOMER COPOLYMER TYPE A; POTASSIUM HYDROXIDE; LAURIC ACID; GLYCERIN; GLYCOL DISTEARATE; LAURAMINE OXIDE; SODIUM METHYL COCOYL TAURATE; PHENOXYETHANOL; BENZOIC ACID; ETHYLHEXYLGLYCERIN; GLYCERETH-2 COCOATE; EDETATE DISODIUM; EUCALYPTUS GLOBULUS LEAF; ZINGIBER OFFICINALE WHOLE; GAULTHERIA PROCUMBENS LEAF; AVENA SATIVA WHOLE; ALLANTOIN; GOAT MILK

DUAL-SHAVE - BOD (71295-104)

ACTIVE INGREDIENT

BENZOYL PEROXIDE 5%

PURPOSE

ACNE TREATMENT

USE

FOR THE TREATMENT OF ACNE AND TO PREVENT SKIN BLEMISHES WHEN SHAVING.

WARNINGS

FOR EXTERNAL USE ONLY.

WHEN USING THIS PRODUCT: SKIN DRYNESS AND IRRITATION IS MORE LIKELY TO OCCUR WHEN USED WITH ANOTHER TOPICAL ACNE MEDICATION AT THE SAME TIME. IF IRRITATION DOES OCCUR, USE LESS ACNE-FIGHTING MEDICATION. ALWAYS TRY TO AVOID ADDED UNNECESSARY SUN EXPOSURE AND ALWAYS USE SUNSCREEN IF POSSIBLE. AVOID CONTACT WITH EYES, LIPS AN MOUTH. IF CONTACT OCCURS FLUSH THOROUGHLY WITH WATER. SKIN IRRITATION IS DEFINED BY SYMPTOMS SUCH AS BURNING, ITCHING, PEELING, SWELLING OR REDNESS. IF BY CHANCE IRRITATION DOES OCCUR, REDUCE IRRITATION BY USING A SMALLER AMOUNT OR BY USING THIS PRODUCT LESS OFTEN.

DO NOT USE

WHEN NOT TO USE THIS PRODUCT: IF YOU HAVE EXTREMELY SENSITIVE SKIN OR ARE HIGHLY SENSITIVE TO BENZOYL PEROXIDE.

STOP USE AND ASK A DOCTOR IF: IRRITATION BECOMES ACUTE.

KEEP OUT OF REACH OF CHILDREN: IF SWALLOWED, SEEK IMMEDIATE MEDICAL ATTENTION OR CONTACT A POISON CONTROL CENTER NEAR YOU.

DIRECTIONS

BOD IS UNLIKE OTHER CLEANSING COAPS, GELS OR FOAMS ON THE MARKET TODAY! THIS FOAMLESS CLEANSER IS BEST USED WHEN WASHING ONE'S BODY & BODY-PARTS IN THE SHOWER. BOD CAN ALSO BE USED IN CONJUNCTION WITH ANOTHER BODY WASHES WHICH DO NOT FIGHT ACNE. IT'S ALWAYS BEST TO WET AREAS WITH WARM WATER TO OPEN THE PORES OF THE SKIN. MAKE SURE YOU RINSE THOROUGHLY.

TIPS: IT IS BEST TO USE A WHITE TOWEL BECAUSE THE ACTIVE INGREDIENT IN THIS PRODUCT BENZOYL PEROXIDE IS KNOWN TO BLEACH COLORED MATERIALS. WHEN WASHING TOWELS WASH WITH WHITE ONLY IN CASE ORF LEFTOVER RESIDUE SO IT DOES NOT AFFECT COLOR MATERIALS.

OTHER INFORMATION

STORE AT 20°C TO 25°C (68°F - 77°F).

INACTIVE INGREDIENTS

WATER, MYRISTIC ACID, SODIUM C14-16 OLEFIN SULFONATE, COCAMIDOPROPYL BETAINE, STEARIC ACID, ACRYLATES COPOLYMER, POTASSIUM HYDROXIDE, LAURIC ACID, GLYCERIN, GLYCOL DISTEARATE, LAURAMINE OXIDE, SODIUM METHYL COCOYL TAURATE, PHENOXYETHANOL, BENZOIC ACID, ETHYLHEXYLGLYCERIN, GLYCERETH-2 COCOATE, FRAGRANCE, DISODIUM EDTA, EUCALYPTUS GLOBULUS LEAF EXTRACT, ZINGIBER OFFICINALE (GINGER) ROOT EXTRACT, GAULTHERIA PROCUMBENS (WINTERGREEN) LEAF EXTRACT, AVENA SATIVA (OAT) KERNEL EXTRACT, ALLANTOIN, GOAT MILK

QUESTIONS?

CALL DIRECT +1 (310) 461-1980 OR VISIT WWW.DUAL-SHAVE.COM